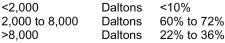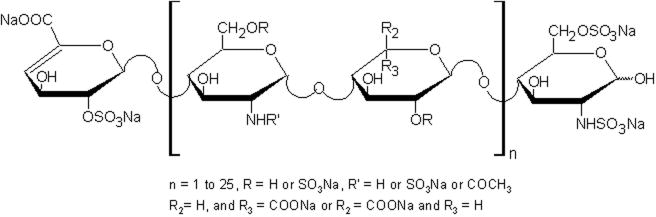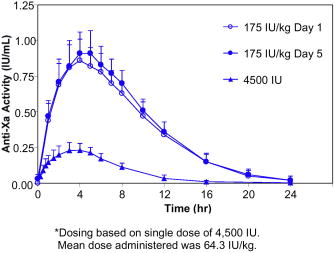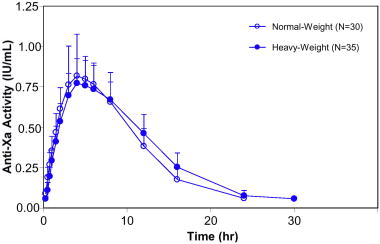 DRUG LABEL: Unknown
Manufacturer: Celgene Corporation
Category: prescription | Type: HUMAN PRESCRIPTION DRUG LABELING
Date: 20080414

INNOHEP®
(tinzaparin sodium injection)

For Subcutaneous (SC) Use Only

SPINAL/EPIDURAL HEMATOMAS

When neuraxial anesthesia (epidural/spinal anesthesia) or spinal puncture is employed, patients anticoagulated or scheduled to be anticoagulated with low molecular weight heparins or heparinoids for prevention of thromboembolic complications are at risk of developing an epidural or spinal hematoma which can result in long-term or permanent paralysis.

The risk of these events is increased by the use of indwelling epidural catheters for administration of analgesia or by the concomitant use of drugs affecting hemostasis such as non-steroidal anti-inflammatory drugs (NSAIDs), platelet inhibitors, or other anticoagulants. The risk also appears to be increased by traumatic or repeated epidural or spinal puncture.

Patients should be frequently monitored for signs and symptoms of neurological impairment. If neurological compromise is noted, urgent treatment is necessary.

The physician should consider the potential benefit versus risk before neuraxial intervention in patients anticoagulated or to be anticoagulated for thromboprophylaxis (see also WARNINGS, Hemorrhage, and PRECAUTIONS, Drug Interactions).

DESCRIPTION

INNOHEP® is a sterile solution, containing tinzaparin sodium, a low molecular weight heparin. It is available in a multiple dose 2 mL vial.

Each 2 mL vial contains 20,000 anti-Factor Xa IU (anti-Xa) of tinzaparin sodium per mL, for a total of 40,000 IU, and 3.1 mg/mL sodium metabisulfite as a stabilizer. The vial contains 10 mg/mL benzyl alcohol as a preservative. Sodium hydroxide may be added to achieve a pH range of 5.0 to 7.5.

Table 1 Composition of 20,000 anti-Xa IU/mL INNOHEP® (tinzaparin sodium injection)
Component | Quantity per mL
Tinzaparin sodium | 20,000 anti-Xa IU
Benzyl alcohol, USP | 10 mg
Sodium metabisulfite, USP | 3.106 mg^1
Sodium hydroxide, USP | as necessary
Water for Injection, USP | q.s. to 1 mL
^1 Corresponding to 3.4 mg/mL sodium bisulfite

Tinzaparin sodium is the sodium salt of a low molecular weight heparin obtained by controlled enzymatic depolymerization of heparin from porcine intestinal mucosa using heparinase from Flavobacterium heparinum. The majority of the components have a 2-O-sulpho-4-enepyranosuronic acid structure at the non-reducing end and a 2-N,6-O-disulpho-D-glucosamine structure at the reducing end of the chain.

Potency is determined by means of a biological assay and interpreted by the first International Low Molecular Weight Heparin Standard as units of anti-factor Xa (anti-Xa) activity per milligram. The mean tinzaparin sodium anti-factor Xa activity is approximately 100 IU per milligram. The average molecular weight ranges between 5,500 and 7,500 daltons. The molecular weight distribution is:

Structural Formula

CLINICAL PHARMACOLOGY

Tinzaparin sodium is a low molecular weight heparin with antithrombotic properties. Tinzaparin sodium inhibits reactions that lead to the clotting of blood including the formation of fibrin clots, both in vitro and in vivo. It acts as a potent co-inhibitor of several activated coagulation factors, especially Factors Xa and IIa (thrombin). The primary inhibitory activity is mediated through the plasma protease inhibitor, antithrombin.

Bleeding time is usually unaffected by tinzaparin sodium. Activated partial thromboplastin time (aPTT) is prolonged by therapeutic doses of tinzaparin sodium used in the treatment of deep vein thrombosis (DVT). Prothrombin time (PT) may be slightly prolonged with tinzaparin sodium treatment but usually remains within the normal range. Neither aPTT nor PT can be used for therapeutic monitoring of tinzaparin sodium.

Neither unfractionated heparin nor tinzaparin sodium have intrinsic fibrinolytic activity; therefore, they do not lyse existing clots. Tinzaparin sodium induces release of tissue factor pathway inhibitor, which may contribute to the antithrombotic effect. Heparin is also known to have a variety of actions that are independent of its anticoagulant effects. These include interactions with endothelial cell growth factors, inhibition of smooth muscle cell proliferation, activation of lipoprotein lipase, suppression of aldosterone secretion, and induction of platelet aggregation.

Pharmacokinetics/Pharmacodynamics

Anti-Xa and anti-IIa activities are the primary biomarkers for assessing tinzaparin sodium exposure because plasma concentrations of low molecular weight heparins cannot be measured directly. Because of analytical assay limitations, anti-Xa activity is the more widely used biomarker. The measurements of anti-Xa and anti-IIa activities in plasma serve as surrogates for the concentrations of molecules which contain the high-affinity binding site for antithrombin (anti-Xa and anti-IIa activities). Monitoring patients based on anti-Xa activity is generally not advised. The data are provided in Figure 1 and Table 2. below.

Studies with tinzaparin sodium in healthy volunteers and patients have been conducted with both fixed- and weight-adjusted dose administration. Recommended therapy with tinzaparin sodium is based on weight-adjusted dosing (see DOSAGE AND ADMINISTRATION).

Figure 1. Mean and Standard Deviation of Anti-Xa Activity Following SC Administration of a Single 4,500 IU* dose and Once Daily Multiple SC Dose of 175 IU/kg Tinzaparin Sodium to Healthy Volunteers

Table 2 Summary of Pharmacokinetic Parameters (Mean and Standard Deviation) Based on Anti-Xa Activity Following Single and Once Daily Multiple Dose SC Administration of Tinzaparin Sodium to Healthy Volunteers
Parameter (Units) | Single Dose (N=23) | Multiple Dose (N=14)
 | 4,500 IU* | Day 1 (175 IU/kg) | Day 5 (175 IU/kg)
Cmax (IU/mL) | 0.25 (0.05) | 0.87 (0.15) | 0.93 (0.15)
Tmax (hr) | 3.7 (0.9) | 4.4 (0.7) | 4.6 (1.0)
AUC0‑∞(IU*hr/mL) | 2.0 (0.5) | 9.0 (1.1) | 9.7 (1.4)
Half-life (hr) | 3.4 (1.7) | 3.3 (0.8) | 3.5 (0.6)
*Dosing based on single dose of 4,500 IU. Mean dose administered was 64.3 IU/kg.

Absorption

Plasma levels of anti-Xa activity increase in the first 2 to 3 hours following SC injection of tinzaparin sodium and reach a maximum within 4 to 5 hours. Maximum concentrations (Cmax) of 0.25 and 0.87 IU/mL are achieved following a single SC fixed dose of 4,500 IU (approximately 64.3 IU/kg) and weight-adjusted dose of 175 IU/kg of tinzaparin sodium, respectively. Based on the extent of absorption (AUC0‑∞), a comparison of 4,500 IU and 12,250 IU single doses indicates that increases in anti-Xa activity are greater than dose proportional relative to the increase in dose. Following a single SC injection of tinzaparin sodium, the mean anti-Xa to anti-IIa activity ratio, based on the area under the anti-Xa and anti-IIa time profiles, is 2.8 and is higher than that of unfractionated heparin (approximately 1.2). The absolute bioavailability (following 4,500 IU SC and intravenous [IV] administrations) is 86.7% based on anti-Xa activity.

Distribution

The volume of distribution of tinzaparin sodium ranges from 3.1 L to 5.0 L. These values are similar in magnitude to blood volume, suggesting that the distribution of anti-Xa activity is limited to the central compartment.

Metabolism

Low molecular weight heparins are partially metabolized by desulphation and depolymerization.

Elimination

In healthy volunteers, the elimination half-life following SC administration of 4,500 IU or 175 IU/kg tinzaparin sodium is approximately 3-4 hours based on anti-Xa activity. Clearance following IV administration of 4,500 IU tinzaparin sodium is approximately 1.7 L/hr. The primary route of elimination is renal. Anti-Xa activity did not accumulate with once daily dosing of 175 IU/kg for five days in healthy volunteers. (See Figure 1 and Table 2.)

Special Populations

Population Pharmacokinetics

Anti-Xa concentrations from approximately 180 patients receiving SC tinzaparin sodium once daily (175 IU/kg body weight) as the treatment of proximal DVT and approximately 240 patients undergoing elective hip replacement surgery receiving SC tinzaparin sodium once daily (~65 IU/kg body weight) were analyzed by population pharmacokinetic methods. The results indicate that neither age nor gender significantly alter tinzaparin sodium clearance based on anti-Xa activity (see PRECAUTIONS, General). However, a reduction in tinzaparin sodium clearance was observed in patients with impaired renal function (reduced calculated creatinine clearance) (see Special Populations, Renal Impairment). Weight is also an important factor for the prediction of tinzaparin sodium clearance, consistent with the recommendation that INNOHEP® therapy be based on weight-adjusted dosing (see DOSAGE AND ADMINISTRATION).

Renal Impairment

Population Pharmacokinetics

In patients being treated with tinzaparin sodium (175 IU/kg) for DVT, a population pharmacokinetic (PK) analysis determined that tinzaparin sodium clearance based on anti-Xa activity was related to creatinine clearance calculated by the Cockroft Gault equation. In this PK analysis, a reduction in tinzaparin sodium clearance in moderate (30-50 mL/min) and severe (<30 mL/min) renal impairment was observed. Patients with severe renal impairment exhibited a 24% reduction in tinzaparin sodium clearance relative to patients with normal renal function (>80 mL/min).

Hemodialysis Studies

In a study of 12 chronic renal failure patients undergoing hemodialysis, anti-Xa clearance was reduced 28%, consistent with estimates from the population PK analyses. In another study of 6 patients undergoing hemodialysis, the half-life of anti-Xa activity following a single IV dose of 75 IU/kg of tinzaparin sodium on an off-dialysis day was prolonged relative to that for healthy volunteers (5.2 versus 1.6 hours).

Patients with severe renal impairment should be dosed with caution (see PRECAUTIONS). Patients aged 90 years or older with creatinine clearance ≤ 60 mL/min should not be treated with INNOHEP® (see CONTRAINDICATIONS).

Hepatic Impairment

No prospective studies have assessed tinzaparin sodium pharmacokinetics or pharmacodynamics in hepatically-impaired patients. However, the hepatic route is not a major route of elimination of low molecular weight heparins (see WARNINGS, Hemorrhage).

Elderly

Since renal function declines with age, elimination of tinzaparin sodium may be reduced in elderly patients. In a prospective study of 30 elderly patients [6 men, 24 women; aged 87.0 ± 5.9 years; mean body weight 62.7 ± 14.6 kg; creatinine clearance 40.6 ± 15.3 mL/min (range 20-72)] treated with tinzaparin sodium 175 IU/kg once daily for ten days for acute venous thromboembolism, there was no accumulation of anti-Xa activity based on peak anti-Xa activity levels.

A phase III/IV clinical study (IRIS; INNOHEP® in Renal Insufficiency Study) compared INNOHEP® (175 IU/kg once daily) and unfractionated heparin (UFH) in the initial treatment of deep vein thrombosis (DVT) and/or pulmonary embolism (PE) in elderly patients with renal insufficiency (i.e., patients aged 70 years or older with estimated creatinine clearance of ≤ 30 mL/min calculated by the Cockcroft Gault formula or patients aged 75 years or older with estimated creatinine clearance of ≤ 60 mL/min). Oral anticoagulants were co-administered beginning on Days 1-3 and study treatment was continued for at least 5 days until INR was between 2-3 on 2 successive days; oral anticoagulants were then continued alone and patients were followed until 90 days after treatment start. An interim analysis of this ongoing study with INNOHEP® indicates that patients aged 90 years or older with renal insufficiency have an increased mortality. Based on this finding, patients aged 90 years or older with creatinine clearance ≤ 60 mL/min should not be treated with INNOHEP® (see CONTRAINDICATIONS).

Obesity

Based on the results of a prospective clinical study and the population PK analyses, weight-based dosing is appropriate for heavy/obese patients. Tinzaparin sodium PK parameters based on anti-Xa activity are independent of body weight and body mass index (BMI) when tinzaparin sodium is dosed on a weight basis at 175 IU/kg or 75 IU/kg. In a prospective study of heavy/obese subjects (101 to 165 kg; BMI 26‑61 kg/m^2), anti-Xa activity time profiles were similar to those in normal-weight volunteer studies. Data at the 175 IU/kg dose are shown in Figure 2. Clinical trial experience is limited in patients with a BMI >40 kg/m^2.

Figure 2 Mean and Standard Deviation of Anti-Xa Activity Following a Single SC Administration of 175 IU/kg Tinzaparin Sodium to Obese Subjects and Normal-Weight Volunteers

Pregnancy

The disposition of INNOHEP® was studied in 54 pregnant patients in any trimester. In this open-label, prospective, dose finding study, those treated with an INNOHEP® dose of 175 IU/kg had similar 24-hour anti-Xa curves at 28 (n=17) and 36 (n=20) weeks gestation. The 175 IU/kg dose resulted in a mean anti-Xa level of 0.3 to 1.0 IU/mL 4 hours after administration. Mean anti-Xa levels 4 hours post dose suggest that as pregnancy advances there is no clinically significant decrease in anti-Xa levels. Pregnancy has little or no influence on the pharmacokinetics of INNOHEP® and no dosing adjustment is needed for pregnancy. (See Dosage And Administration.)

CLINICAL STUDIES

Treatment of Acute Deep Vein Thrombosis (DVT) With or Without Pulmonary Embolism (PE)

In a randomized, multicenter, double-blind trial INNOHEP® (tinzaparin sodium injection) was compared to unfractionated heparin in 435 hospitalized patients with symptomatic, proximal DVT. Six percent of the enrolled patients had symptomatic pulmonary embolism confirmed by segmental or greater lung scan defect. The study patients ranged in age from 19 to 92 years (mean 61 ± 17 years), 55% were male, 88% were white and 8% black. Patients received either INNOHEP® SC once daily according to body weight (175 IU/kg) and a placebo IV bolus followed by continuous placebo IV infusion, or unfractionated heparin as an initial IV bolus dose (5,000 IU) followed by continuous IV infusion of unfractionated heparin with the rate adjusted according to the aPTT (1.5 to 2.5 times control value) and a once daily SC placebo injection. Treatment continued for approximately 6 days, and both treatment groups also received oral warfarin sodium starting on Day 2 which continued to Day 90 with doses titrated to a target INR of 2.0 to 3.0.

The 90-day cumulative thromboembolic (TE) rate [recurrent DVT or PE] with INNOHEP® was not significantly different than the rate with unfractionated heparin. The data are provided in Table 3.

Table 3 Efficacy of Once Daily INNOHEP® in the Treatment of Acute Deep Vein Thrombosis
 | Dosing Regimen
Indication | INNOHEP®^1 175 IU/kg Once Daily SC n (%) | Heparin^1 5,000 IU Bolus then aPTT Adjusted Continuous Infusion IV n (%)
Treatment of Acute DVT | INNOHEP®^1 175 IU/kg Once Daily SC n (%) | Heparin^1 5,000 IU Bolus then aPTT Adjusted Continuous Infusion IV n (%)
Intent to Treat Population^2 | 216 (100%) | 219 (100%)
Patient Outcome at 90 Days
Total TE^3 Events | 6 (2.8%)^4 | 15 (6.8%)^4
DVTs | 3 (1.4%) | 9 (4.1%)
PEs | 3 (1.4%) | 6 (2.7%)
^1 Patients were also treated with warfarin sodium commencing within 24-48 hours of tinzaparin sodium or standard heparin therapy.
^2 All randomized patients who received at least one dose of active study drug
^3 TE = thromboembolic events (DVT and/or PE)
^4 The 95% Confidence Interval (CI) for the total TE event rate difference (4.0%) was 0.07%, 8.07%.

Mortality with INNOHEP® was 4.6% (10 patients) and with heparin 9.6% (21 patients). The 95% confidence interval (CI) for the mortality difference was 0.16%, 9.76%.

In a multicenter, open-label, randomized clinical trial INNOHEP® was compared to unfractionated heparin as initial treatment for hospitalized patients with symptomatic PE not requiring thrombolytic therapy, embolectomy, or vena cava interruption. Patients were excluded if they carried an unusually high risk for thromboembolic and/or bleeding events or other complications. Of the 608 patients treated, 422 had documented DVT. Prior to determination of study eligibility and randomization, patients were allowed to receive unfractionated heparin; 78% of the patients received unfractionated heparin at therapeutic doses for up to 24 hours, and an additional 4% received heparin at therapeutic doses for greater than 24 hours. After randomization, INNOHEP® was administered SC once daily, 175 IU/kg body weight; heparin as an initial IV bolus (50 IU/kg) followed by continuous IV infusion with the rate adjusted according to the aPTT (2 to 3 times control value). For both groups, treatment continued for approximately 8 days. All patients also received oral anticoagulant treatment starting in the first 3 days which continued to Day 90.

Thromboembolic events were infrequent for both treatment groups. No difference was observed between the two treatment groups for incidence of recurrence of thromboembolic events.

INDICATIONS AND USAGE

INNOHEP® is indicated for the treatment of acute symptomatic deep vein thrombosis with or without pulmonary embolism when administered in conjunction with warfarin sodium. The safety and effectiveness of INNOHEP® were established in hospitalized patients.

CONTRAINDICATIONS

INNOHEP® is contraindicated in patients with active major bleeding, in patients with (or history of) heparin-induced thrombocytopenia, or in patients with hypersensitivity to tinzaparin sodium.

INNOHEP® is contraindicated in patients aged 90 years or older with creatinine clearance ≤ 60 mL/min.

Patients with known hypersensitivity to heparin, sulfites, benzyl alcohol, or pork products should not be treated with INNOHEP®.

WARNINGS

INNOHEP® is not intended for intramuscular or intravenous administration.

INNOHEP® cannot be used interchangeably (unit for unit) with heparin or other low molecular weight heparins as they differ in manufacturing process, molecular weight distribution, anti-Xa and anti-IIa activities, units, and dosage. Each of these medications has its own instructions for use.

INNOHEP® should not be used in patients with a history of heparin-induced thrombocytopenia (see CONTRAINDICATIONS).

Hemorrhage: INNOHEP®, like other anticoagulants, should be used with extreme caution in conditions with increased risk of hemorrhage, such as bacterial endocarditis; severe uncontrolled hypertension; congenital or acquired bleeding disorders including hepatic failure and amyloidosis; active ulcerative and angiodysplastic gastrointestinal disease; hemorrhagic stroke; shortly after brain, spinal or ophthalmological surgery, or in patients treated concomitantly with platelet inhibitors. Bleeding can occur in any tissue or organ of the body during therapy with INNOHEP®. Hemorrhage in some cases has been reported to result in death or permanent disability. A hemorrhagic event should be seriously considered in the presence of an unexplained fall in hematocrit, hemoglobin, or blood pressure. If severe hemorrhage occurs, INNOHEP® should be discontinued.

Spinal or epidural hematomas can occur with the associated use of low molecular weight heparins or heparinoids and spinal/epidural anesthesia or spinal puncture which can result in long-term or permanent paralysis. The risk of these events is higher with the use of post-operative indwelling epidural catheters or with the concomitant use of additional drugs affecting hemostasis such as NSAIDs (see boxed WARNING and PRECAUTIONS, Drug Interactions).

Thrombocytopenia: Thrombocytopenia can occur with the administration of INNOHEP®.

In clinical studies, thrombocytopenia (platelet count <100,000/mm^3 if baseline value ≥150,000/mm^3, ≥50% decline if baseline <150,000/mm^3) was identified in 1% of patients given INNOHEP®; severe thrombocytopenia (platelet count less than 50,000/mm^3) occurred in 0.13%.

Thrombocytopenia of any degree should be monitored closely. If the platelet count falls below 100,000/mm^3, INNOHEP® should be discontinued. Cases of thrombocytopenia with disseminated thrombosis also have been observed in clinical practice with heparins, and low molecular weight heparins, including tinzaparin sodium. Some of these cases were complicated by organ infarction with secondary organ dysfunction or limb ischemia, and have resulted in death.

Hypersensitivity: INNOHEP® contains sodium metabisulfite, a sulfite that may cause allergic-type reactions including anaphylactic symptoms and life-threatening asthmatic episodes in certain susceptible people. The overall prevalence of sulfite sensitivity in the general population is unknown, but is probably low. Sulfite sensitivity is more frequent in asthmatic people than in non-asthmatic people.

Priapism: Priapism has been reported from post-marketing surveillance as a rare occurrence. In some cases surgical intervention was required.

Miscellaneous: INNOHEP® multiple dose vial contains benzyl alcohol as a preservative. The administration of medications containing benzyl alcohol as a preservative to premature neonates has been associated with a fatal “Gasping Syndrome." Because benzyl alcohol may cross the placenta, INNOHEP® preserved with benzyl alcohol should be used with caution in pregnant women only if clearly needed (see PRECAUTIONS, Pregnancy).

PRECAUTIONS

GENERAL PRECAUTIONS

General: INNOHEP® should not be mixed with other injections or infusions.

INNOHEP® should be used with care in patients with a bleeding diathesis, uncontrolled arterial hypertension, or a history of recent gastrointestinal ulceration, diabetic retinopathy, and hemorrhage.

Consistent with expected age-related changes in renal function, elderly patients and patients with renal insufficiency may show reduced elimination of tinzaparin sodium. INNOHEP® should be used with care in these patients (see CLINICAL PHARMACOLOGY, Special Populations). Patients aged 90 years or older with creatinine clearance ≤ 60 mL/min should not be treated with INNOHEP® (see CONTRAINDICATIONS).

LABORATORY TESTS

Laboratory Tests: Periodic complete blood counts including platelet count and hematocrit or hemoglobin, and stool tests for occult blood are recommended during treatment with INNOHEP®. When administered at the recommended doses, routine anticoagulation tests such as prothrombin time (PT) and activated partial thromboplastin time (aPTT) are relatively insensitive measures of INNOHEP® activity and, therefore, are unsuitable for monitoring.

DRUG INTERACTIONS

Drug Interactions: Because of increased risk of bleeding, INNOHEP® should be used with caution in patients receiving oral anticoagulants, platelet inhibitors (e.g., salicylates, dipyridamole, sulfinpyrazone, dextran, NSAIDs including ketorolac tromethamine, ticlopidine, and clopidogrel), and thrombolytics. If coadministration is essential, close clinical and laboratory monitoring of these patients is advised (see PRECAUTIONS, Laboratory Tests).

Laboratory Test Interactions

Elevation of Serum Transaminases: Asymptomatic reversible increases in aspartate (AST [SGOT]) and alanine (ALT [SGPT]) aminotransferase levels have occurred in patients during treatment with INNOHEP® (see ADVERSE REACTIONS, Elevations of Serum Aminotransferases). Similar increases in transaminase levels have also been observed in patients and volunteers treated with heparin and other low molecular weight heparins.

Since aminotransferase determinations are important in the differential diagnosis of myocardial infarction, liver disease, and pulmonary emboli, elevations that might be caused by drugs like INNOHEP® should be interpreted with caution.

CARCINOGENESIS AND MUTAGENESIS AND IMPAIRMENT OF FERTILITY

Carcinogenesis, Mutagenesis, Impairment of Fertility: No long-term studies in animals have been performed to evaluate the carcinogenic potential of tinzaparin sodium.

Tinzaparin sodium displayed no genotoxic potential in an in vitro bacterial cell mutation assay (AMES test), in vitro Chinese hamster ovary cell forward gene mutation test, in vitro human lymphocyte chromosomal aberration assay, and in vivo mouse micronucleus assay. Tinzaparin sodium at SC doses up to 1800 IU/kg/day in rats (about 2 times the maximum recommended human dose based on body surface area) was found to have no effect on fertility and reproductive performance.

Pregnancy

Pregnancy: Category B:

All pregnancies have a background risk of birth defects, loss, or other adverse outcome regardless of drug exposure. The fetal risk summary below describes the potential of INNOHEP® to increase the risk of developmental abnormalities above background risk.

Fetal Risk Summary

INNOHEP® is not predicted to increase the risk of developmental abnormalities. INNOHEP® does not cross the placenta, based on human and animal studies, and shows no evidence of teratogenic effects or fetotoxicity.

Clinical Considerations

Pregnancy alone confers an increased risk for thromboembolism that is even higher for women with preexisting thromboembolic disease, certain high risk pregnancy conditions, and a history of complications during a previous pregnancy.

All patients receiving anticoagulants such as tinzaparin, including pregnant women, are at risk for bleeding. Pregnant women receiving tinzaparin should be carefully monitored for evidence of bleeding or excessive anticoagulation. Hemorrhage can occur at any site and may lead to death of mother and/or fetus. Pregnant women should be apprised of the potential hazard to the fetus and the mother if tinzaparin is administered during pregnancy. Consideration for use of a shorter acting agent should be specifically addressed as delivery approaches.

Data

Human Data - Fifty-four women pregnant or planning to become pregnant with conditions requiring anticoagulation received INNOHEP® in an open-label, prospective, pregnancy dose finding study. (See Clinical Pharmacology, Special Populations, Pregnancy.) Patients received 50 to 175 IU/kg/day, with dosing starting as early as prior to conception or as late as 32 weeks gestation. Duration of exposure ranged from 3 to 463 days (median 159 days). From 55 pregnancies, there were 50 live births, 3 first trimester miscarriages, and 2 intrauterine deaths at 17 and 30 weeks. Approximately 6% of pregnancies were complicated by fetal distress.

Approximately 10% of pregnant women receiving INNOHEP® experienced significant vaginal bleeding. A cause and effect relationship for the above observations has not been established.

Animal Data - Teratogenicity studies have been performed in rats at SC doses up to 1800 IU/kg/day (about 2 times the maximum recommended human dose based on body surface area) and in rabbits at SC doses up to 1900 IU/kg/day (about 4 times the maximum recommended human dose based on body surface area) and have revealed no evidence of impaired fertility or harm to the fetus due to tinzaparin sodium. There are, however, no adequate and well-controlled studies in pregnant women. Because animal reproduction studies are not always predictive of human response, this drug should be used during pregnancy only if clearly needed. INNOHEP® does not cross the placenta.

Cases of "Gasping Syndrome" have occurred in premature infants when large amounts of benzyl alcohol have been administered (99 - 404 mg/kg/day). The 2 mL vial of INNOHEP® contains 20 mg of benzyl alcohol (10 mg of benzyl alcohol per mL) (see WARNINGS, Miscellaneous). If INNOHEP® is used during pregnancy, or if the patient becomes pregnant while taking this drug, the patient should be apprised of potential hazards to the fetus.

NURSING MOTHERS

Nursing Mothers: In studies where tinzaparin sodium was administered subcutaneously to lactating rats, very low levels of tinzaparin sodium were found in breast milk. It is not known whether tinzaparin sodium is excreted in human milk. Because many drugs are excreted in human milk, caution should be exercised when INNOHEP® is administered to nursing women.

PEDIATRIC USE

Pediatric Use: Safety and effectiveness of tinzaparin sodium in pediatric patients have not been established.

GERIATRIC USE

Geriatric Use: In the clinical studies for the treatment of DVT described in the CLINICAL STUDIES section, 58% of patients were 65 or older and 29% were 75 and over. In these studies, no significant overall differences in safety or effectiveness were observed between these subjects and younger subjects. In the interim analysis of an ongoing study (IRIS study) comparing INNOHEP® (175 IU/kg once daily) and unfractionated heparin (UFH) in the initial treatment of deep vein thrombosis (DVT) and/or pulmonary embolism (PE) in elderly patients (75 years or older) with creatinine clearance ≤ 60 mL/min, a higher mortality was observed in patients aged 90 years or older who were treated with INNOHEP® as compared to those treated with unfractionated heparin. Patients aged 90 years or older with creatinine clearance ≤ 60 mL/min should not be treated with INNOHEP® (see CLINICAL PHARMACOLOGY, Special Populations and CONTRAINDICATIONS).

ADVERSE REACTIONS

Bleeding: Bleeding is the most common adverse event associated with INNOHEP® (tinzaparin sodium injection); however, the incidence of major bleeding is low. In clinical trials, the definition of major bleeding included bleeding accompanied by ≥2 gram/dL decrease in hemoglobin, requiring transfusion of 2 or more units of blood products, or bleeding which was intracranial, retroperitoneal, or into a major prosthetic joint. The data are provided in Table 4.

Table 4 Major Bleeding Events^1 in Treatment of Acute Deep Vein Thrombosis With or Without Pulmonary Embolism
Indication | Treatment Group^1
Treatment of Acute DVT With or Without PE | INNOHEP® N=519 % | Heparin N=524 %
Major Bleeding Events^2 | 0.8^3 | 2.7^3
^1 INNOHEP® 175 IU/kg once daily SC. Unfractionated heparin initial IV bolus of 5,000 IU followed by continuous IV infusion adjusted to an aPTT of 1.5 to 2.5 or initial IV bolus of 50 IU/kg followed by continuous IV infusion adjusted to an aPTT of 2.0 to 3.0. In all groups treatment continued for approximately 6 to 8 days, and all patients received oral anticoagulant treatment commencing in the first 2 to 3 days.
^2 Bleeding accompanied by ≥2 gram/dL decline in hemoglobin, requiring transfusion of 2 or more units of blood products, or bleeding which was intracranial, retroperitoneal, or into a major prosthetic joint.
^3 The 95% CI on the difference in major bleeding event rates (1.9%) was 0.33%, 3.47%.

Fatal or nonfatal hemorrhage from any tissue or organ can occur. The signs, symptoms, and severity will vary according to the location and degree or extent of the bleeding. Hemorrhagic complications may present as, but are not limited to, paralysis; paresthesia; headache, chest, abdomen, joint, muscle or other pain; dizziness; shortness of breath, difficult breathing or swallowing; swelling; weakness; hypotension, shock, or coma. Therefore, the possibility of hemorrhage should be considered in evaluating the condition of any anticoagulated patient with complaints which do not indicate an obvious diagnosis (see WARNINGS, Hemorrhage).

Thrombocytopenia: In clinical studies thrombocytopenia was identified in 1% of patients treated with INNOHEP®. Severe thrombocytopenia (platelet count <50,000/mm^3) occurred in 0.13% (see WARNINGS, Thrombocytopenia).

Elevations of Serum Aminotransferases: Asymptomatic increases in aspartate (AST [SGOT]) and/or alanine (ALT [SGPT]) aminotransferase levels greater than 3 times the upper limit of normal of the laboratory reference range have been reported in up to 8.8% and 13% for AST and ALT, respectively, of patients receiving tinzaparin sodium for the treatment of DVT. Similar increases in aminotransferase levels have also been observed in patients and healthy volunteers treated with heparin and other low molecular weight heparins. Such elevations are reversible and are rarely associated with increases in bilirubin (see PRECAUTIONS, Laboratory Tests).

Local Reactions: Mild local irritation, pain, hematoma, and ecchymosis may follow SC injection of INNOHEP®. Injection site hematoma has been reported in approximately 16% of patients treated with INNOHEP®.

Hypersensitivity: Anaphylactic/anaphylactoid reactions may occur in association with INNOHEP® use (see CONTRAINDICATIONS and WARNINGS).

Adverse Events: Adverse events with INNOHEP® or heparin reported at a frequency of ≥1% in clinical trials with patients undergoing treatment for proximal DVT with or without PE, are provided in Table 5.

Table 5 Adverse Events Occurring in ≥ 1% in Treatment of Acute Deep Vein Thrombosis With or Without Pulmonary Embolism Studies
 | Treatment Group^1
Adverse Events | INNOHEP® N=519 n (%) | Heparin N=524 n (%)
Urinary Tract Infection | 19 (3.7%) | 18 (3.4%)
Pulmonary Embolism | 12 (2.3%) | 12 (2.3%)
Chest Pain | 12 (2.3%) | 8 (1.5%)
Epistaxis | 10 (1.9%) | 7 (1.3%)
Headache | 9 (1.7%) | 9 (1.7%)
Nausea | 9 (1.7%) | 10 (1.9%)
Hemorrhage NOS | 8 (1.5%) | 23 (4.4%)
Back Pain | 8 (1.5%) | 2 (0.4%)
Fever | 8 (1.5%) | 11 (2.1%)
Pain | 8 (1.5%) | 7 (1.3%)
Constipation | 7 (1.3%) | 9 (1.7%)
Rash | 6 (1.2%) | 8 (1.5%)
Dyspnea | 6 (1.2%) | 9 (1.7%)
Vomiting | 5 (1.0%) | 8 (1.5%)
Hematuria | 5 (1.0%) | 6 (1.1%)
Abdominal Pain | 4 (0.8%) | 6 (1.1%)
Diarrhea | 3 (0.6%) | 7 (1.3%)
Anemia | 0 | 7 (1.3%)
NOS = not otherwise specified
^1 INNOHEP® 175 IU/kg once daily SC. Unfractionated heparin initial IV bolus of 5,000 IU followed by continuous IV infusion adjusted to an aPTT of 1.5 to 2.5 or initial IV bolus of 50 IU/kg followed by continuous IV infusion adjusted to an aPTT of 2.0 to 3.0. In all groups treatment continued for approximately 6 to 8 days, and all patients received oral anticoagulant treatment commencing in the first 2 to 3 days.

Other Adverse Events in Completed or Ongoing Trials: Other adverse events reported at a frequency of ≥1% in 4,000 patients who received INNOHEP® in completed or ongoing clinical trials are listed by body system:

Body as a Whole: injection site hematoma, reaction unclassified.

Cardiovascular Disorders, General: hypotension, hypertension.

Central and Peripheral Nervous System Disorders: dizziness.

Gastrointestinal System Disorders: flatulence, gastrointestinal disorder (not otherwise specified), dyspepsia.

Heart Rate and Rhythm Disorders: tachycardia.

Myo-, Endo-, Pericardial and Valve Disorders: angina pectoris.

Platelet, Bleeding and Clotting Disorders: hematoma, thrombocytopenia.

Psychiatric Disorders: insomnia, confusion.

Red Blood Cell Disorders: anemia.

Resistance Mechanism Disorders: healing impaired, infection.

Respiratory System Disorders: pneumonia, respiratory disorder.

Skin and Appendages Disorders: rash erythematous, pruritus, bullous eruption, skin disorder.

Urinary System Disorders: urinary retention, dysuria.

Vascular (Extracardiac) Disorders: thrombophlebitis deep, thrombophlebitis leg deep.

Serious adverse events reported in clinical trials or from post-marketing experience are included in Tables 6 and 7, respectively:

Table 6 Serious Adverse Events Associated With INNOHEP® in Clinical Trials
Category | Serious Adverse Event
Bleeding-related | Anorectal bleeding Cerebral/intracranial bleeding Epistaxis Gastrointestinal hemorrhage Hemarthrosis Hematemesis Hematuria Hemopericardium Hemorrhage NOS Injection site bleeding Melena Purpura Retroperitoneal/intra-abdominal bleeding Vaginal hemorrhage Wound hematoma
Organ dysfunction | Angina pectoris Cardiac arrhythmia Dependent edema Myocardial infarction/coronary thrombosis Thromboembolism
Fetal/neonatal | Congenital anomaly Fetal death Fetal distress
Cutaneous | Bullous eruption Erythematous rash Maculopapular rash Skin necrosis
Hematologic | Granulocytopenia Thrombocytopenia
Allergic reactions | Allergic reaction
Injection site reaction | Cellulitis
Neoplastic | Neoplasm

Table 7 Other Serious Adverse Events Associated With INNOHEP® from Post-Marketing Surveillance
Category | Serious Adverse Event
Organ dysfunction | Cholestatic hepatitis Increase in hepatic enzymes Peripheral ischemia Priapism
Bleeding-related | Hematoma Hemoptysis Ocular hemorrhage Rectal bleeding
Cutaneous reactions | Epidermal necrolysis Ischemic necrosis Stevens-Johnson syndrome Urticaria
Hematologic | Agranulocytosis Pancytopenia Thrombocythemia
Injection site reactions | Abscess Necrosis
Allergic reactions | Allergic purpura Angioedema
Fetal/neonatal | Cutis aplasia of the scalp Neonatal hypotonia
General | Acute febrile reaction

Ongoing Safety Surveillance: When neuraxial anesthesia (epidural/spinal anesthesia) or spinal puncture is employed, patients anticoagulated or scheduled to be anticoagulated with low molecular weight heparins or heparinoids for prevention of thromboembolic complications are at risk of developing an epidural or spinal hematoma which can result in long-term or permanent paralysis (see boxed WARNING).

Spinal epidural hematoma with INNOHEP® administered at a therapeutic dose has been reported in at least one patient who had not received neuraxial anesthesia or spinal puncture.

OVERDOSAGE

Symptoms/Treatment: Accidental overdosage of INNOHEP® (tinzaparin sodium injection) may lead to bleeding complications (see WARNINGS, Hemorrhage). Nosebleeds, blood in urine or tarry stools may be noted as the first signs of bleeding. Easy bruising or petechial hemorrhages may precede frank bleeding. In case of minor bleeding, the patient should be monitored for signs of more severe bleeding.

Of patients known to have received an overdose of tinzaparin sodium in clinical trials, defined as one or more doses >200 IU/kg for the treatment of DVT or >100 IU/kg for the prevention of DVT, approximately 16% experienced a bleeding complication.

Of spontaneous reports of probable overdosing with tinzaparin sodium, approximately 81% were accompanied by bleeding, usually hematoma. Most patients who have bleeding complications while receiving INNOHEP® can be controlled by discontinuing INNOHEP®, applying pressure to the site, if possible, and replacing volume and hemostatic blood elements (e.g., red blood cells, fresh frozen plasma, platelets) as required. In the event that this is ineffective, protamine sulfate can be administered.

In cases of serious bleeding or large overdose, protamine sulfate (1% solution) can be given by slow IV infusion at a dose of 1 mg protamine for every 100 anti-Xa IU of INNOHEP® given. A second infusion of 0.5 mg protamine sulfate per 100 anti-Xa IU of INNOHEP® may be administered if the aPTT measured 2 to 4 hours after the first infusion remains prolonged. Even with the additional dose of protamine, the aPTT may remain more prolonged than would usually be found following administration of protamine to reverse unfractionated heparin. Protamine does not completely neutralize tinzaparin sodium anti-Xa activity (maximum about 60%).

Particular care should be taken to avoid overdosage with protamine sulfate. Administration of protamine sulfate can cause severe hypotensive and anaphylactoid reactions. Because fatal reactions have been reported with protamine sulfate, it should be given only when resuscitation facilities are readily available. For additional information consult the labeling of Protamine Sulfate Injection, USP, products.

Single SC doses of tinzaparin sodium at 22,000 and 7,700 IU/kg (about 10 and 7 times the maximum recommended human dose, respectively, based upon body surface area) were lethal to mice and rats, respectively. Symptoms of acute toxicity included hematoma formation and bleeding at the injection site, anemia, decreased motor activity, unsteady gait, piloerection, and ptosis.

DOSAGE AND ADMINISTRATION

All patients should be evaluated for bleeding disorders before administration of INNOHEP®. Since coagulation parameters are unsuitable for monitoring INNOHEP® activity, routine monitoring of coagulation parameters is not required (see PRECAUTIONS, Laboratory Tests).

Adult Dosage

The recommended dose of INNOHEP® for the treatment of DVT with or without PE is 175 anti-Xa IU/kg of body weight, administered SC once daily for at least 6 days and until the patient is adequately anticoagulated with warfarin (INR at least 2.0 for two consecutive days). Warfarin sodium therapy should be initiated when appropriate (usually within 1-3 days of INNOHEP® initiation). Pregnancy has little or no influence on the pharmacokinetics of INNOHEP® and no dosing adjustment is needed for pregnancy.

As INNOHEP® may theoretically affect the PT/INR, patients receiving both INNOHEP® and warfarin should have blood for PT/INR determination drawn just prior to the next scheduled dose of INNOHEP®.

Table 8 provides INNOHEP® doses for the treatment of DVT with or without PE. It is necessary to calculate the appropriate INNOHEP® dose for patient weights not displayed in Table 8.

An appropriately calibrated syringe should be used to assure withdrawal of the correct volume of drug from INNOHEP® vials.

Table 8 INNOHEP® Weight-based Dosing for Treatment of Deep Vein Thrombosis With or Without Symptomatic Pulmonary Embolism
 | DVT Treatment
Patient Body Weight in Pounds | 175 IU/kg SC Once Daily 20,000 IU per mL |  | Patient Body Weight in Kilograms
Patient Body Weight in Pounds | Dose (IU) | Amount (mL) | Patient Body Weight in Kilograms
68-80 | 6,000 | 0.3 | 31-36
81-94 | 7,000 | 0.35 | 37-42
95-107 | 8,000 | 0.4 | 43-48
108-118 | 9,000 | 0.45 | 49-53
119-131 | 10,000 | 0.5 | 54-59
132-144 | 11,000 | 0.55 | 60-65
145-155 | 12,000 | 0.6 | 66-70
156-168 | 13,000 | 0.65 | 71-76
169-182 | 14,000 | 0.7 | 77-82
183-195 | 15,000 | 0.75 | 83-88
196-206 | 16,000 | 0.8 | 89-93
207-219 | 17,000 | 0.85 | 94-99
220-232 | 18,000 | 0.9 | 100-105
233-243 | 19,000 | 0.95 | 106-110
244-256 | 20,000 | 1 | 111-116
257-270 | 21,000 | 1.05 | 117-122
271-283 | 22,000 | 1.1 | 123-128
284-294 | 23,000 | 1.15 | 129-133
295-307 | 24,000 | 1.2 | 134-139
308-320 | 25,000 | 1.25 | 140-145
321-331 | 26,000 | 1.3 | 146-150
332-344 | 27,000 | 1.35 | 151-156
345-358 | 28,000 | 1.4 | 157-162

To calculate the volume (mL) of an INNOHEP® 175 anti-Xa IU per kg SC dose for treatment of deep vein thrombosis:

Patient weight (kg) X 0.00875 mL/kg = volume to be administered (mL) subcutaneously

Administration

INNOHEP® is a clear, colorless to slightly yellow solution, and as with other parenteral drug products should be inspected visually for particulate matter and discoloration prior to administration.

INNOHEP® is administered by SC injection. It must not be administered by intramuscular or intravenous injection.

Subcutaneous Injection Technique: Patients should be lying down (supine) or sitting and INNOHEP® administered by deep SC injection. Administration should be alternated between the left and right anterolateral and left and right posterolateral abdominal wall. The injection site should be varied daily. The whole length of the needle should be introduced into a skin fold held between the thumb and forefinger; the skin fold should be held throughout the injection. To minimize bruising, do not rub the injection site after completion of the injection.

HOW SUPPLIED

INNOHEP® is available in a multiple dose 2 mL vial in the following packages:

Box of 1 | 2 mL vial (20,000 anti-Xa IU per mL)
 | NDC 67211-342-08
Box of 10 | 2 mL vials (20,000 anti-Xa IU per mL)
 | NDC 67211-342-53

Store at 25° C (77° F); excursions permitted to 15°-30° C (59°-86° F) [See USP Controlled Room Temperature].

Keep out of the reach of children.

MANUFACTURED FOR:
Celgene Corporation
Boulder, CO 80301

MANUFACTURED BY:
LEO Pharmaceutical Products
DK-2750 Ballerup, Denmark

Innohep® is a registered trademark of LEO Pharmaceutical Products.

April 2008